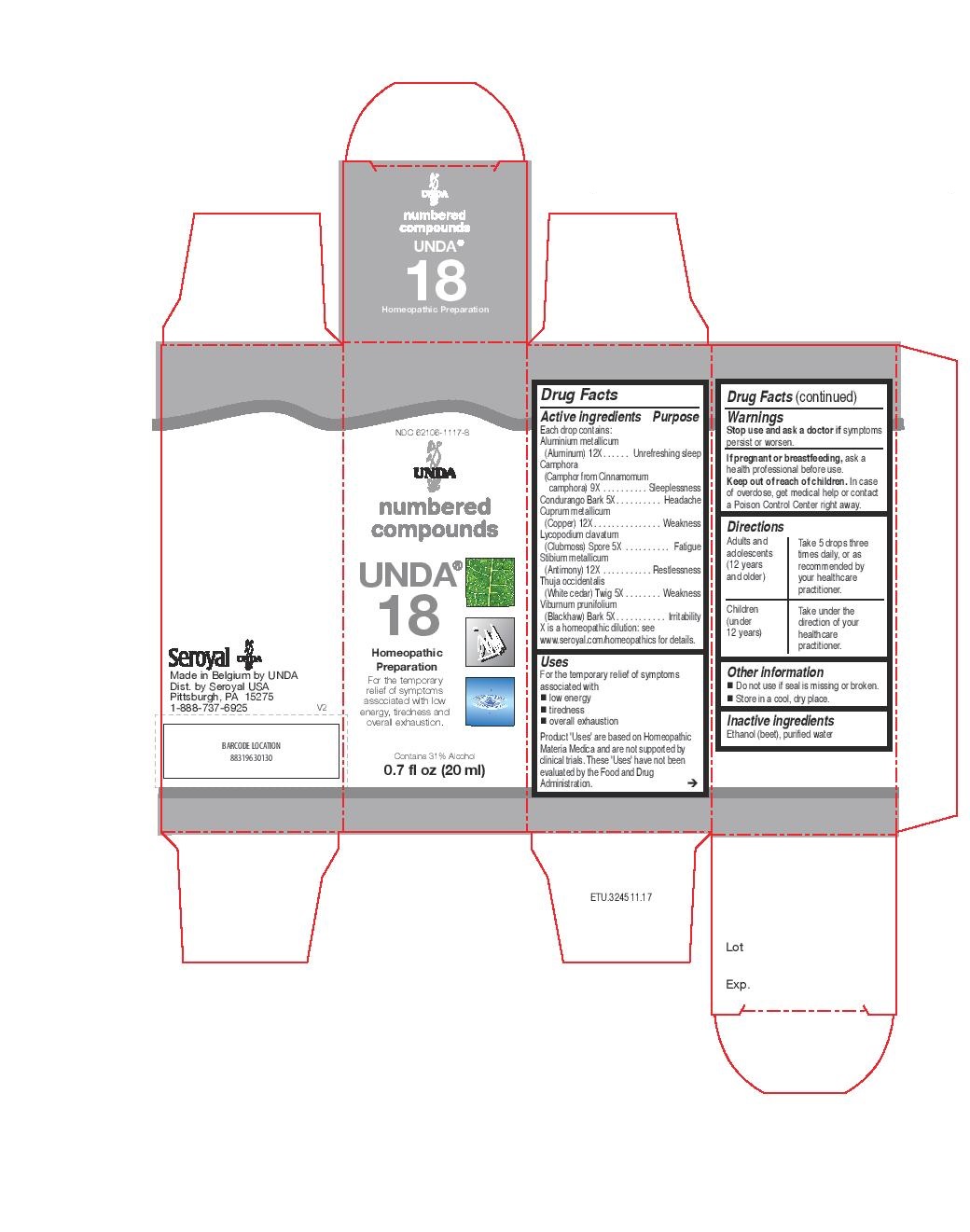 DRUG LABEL: Unda 18
NDC: 62106-1117 | Form: LIQUID
Manufacturer: Seroyal USA
Category: homeopathic | Type: HUMAN OTC DRUG LABEL
Date: 20221109

ACTIVE INGREDIENTS: ANTIMONY 12 [hp_X]/20 mL; MARSDENIA CONDURANGO BARK 5 [hp_X]/20 mL; VIBURNUM PRUNIFOLIUM BARK 5 [hp_X]/20 mL; THUJA OCCIDENTALIS LEAFY TWIG 5 [hp_X]/20 mL; CINNAMOMUM CAMPHORA WHOLE 9 [hp_X]/20 mL; COPPER 12 [hp_X]/20 mL; LYCOPODIUM CLAVATUM SPORE 5 [hp_X]/20 mL; ALUMINUM 12 [hp_X]/20 mL
INACTIVE INGREDIENTS: ALCOHOL; WATER

UNDA 18

Active ingredients
Each drop contains:
Aluminium metallicum (Aluminum) 12X
Camphora (Camphor from Cinnamomum camphora) 9X
Condurango Bark 5X
Cuprum metallicum (Copper) 12X
Lycopodium clavatum (Clubmoss) Spore 5X
Stibium metallicum (Antimony) 12X
Thuja occidentalis (White cedar) Twig 5X
Viburnum prunifolium (Blackhaw) Bark 5X

Uses
For the temporary relief of symptoms associated with
low energy
tiredness
overall exhaustion

Warnings
Stop use and ask a doctor if symptoms persist or worsen.
If pregnant or breastfeeding, ask a health professional before use.

Keep out of reach of children.

In case of overdose, get medical help or contact a
Poison Control Center right away.

PREGNANCY OR BREAST FEEDING

If pregnant or breastfeeding, ask a health professional before use.

Keep out of reach of children.

OVERDOSAGE

In case of overdose, get medical help or contact a

Poison Control Center right away.

Stop use and ask a doctor if symptoms persist or worsen.

Inactive ingredients
Ethanol (beet), purified water

Directions
Adults and adolescents (12 years and older)

Take 5 drops three times daily, or as recommended by your healthcare practitioner.

Children (under 12 years)

Take under the direction of your healthcare practitioner.

Uses
For the temporary relief of symptoms associated with
low energy
tiredness
overall exhaustion

Directions
Adults and adolescents (12 years and older)

Take 5 drops three times daily, or as recommended by your healthcare practitioner.

Children (under 12 years)

Take under the direction of your healthcare practitioner.

PACKAGE LABEL

NDC 62106-1117-8

UNDA

numbered compounds

UNDA 18

Homeopathic Preparation

For the temporary relief of symptoms associated with low energy, tiredness and overall exhaustion.

Contains 31% Alcohol
0.7 fl oz (20 ml)